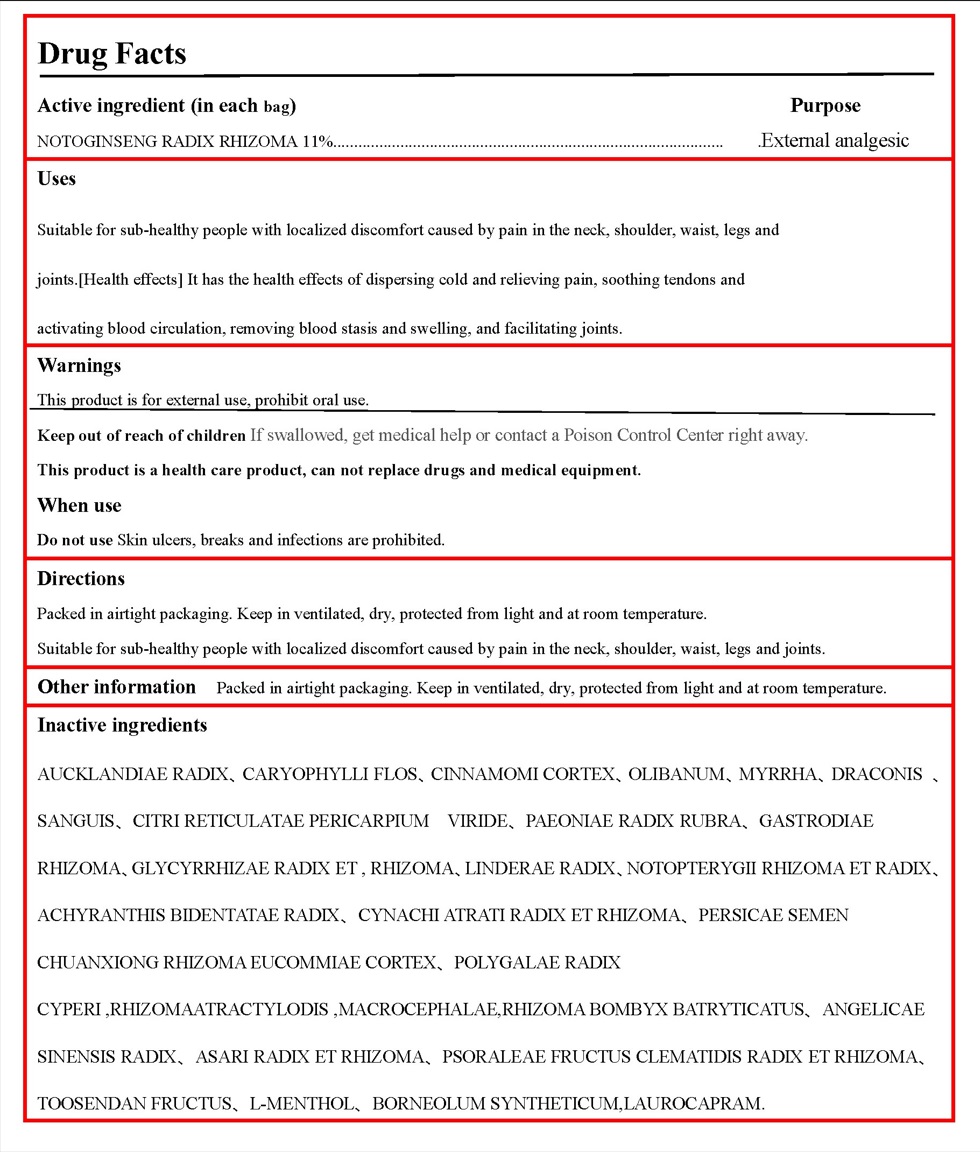 DRUG LABEL: Knee Joint Patch
NDC: 52784-022 | Form: PATCH
Manufacturer: ZHENGZHOU GIANT BIOCHEMISTRY GROUP CO.,LTD
Category: otc | Type: HUMAN OTC DRUG LABEL
Date: 20231219

ACTIVE INGREDIENTS: PANAX NOTOGINSENG ROOT 11 g/100 g
INACTIVE INGREDIENTS: NOTOPTERYGIUM INCISUM ROOT; ACHYRANTHES BIDENTATA ROOT; MELIA AZEDARACH FRUIT; DRAGON'S BLOOD; LICORICE; LINDERA AGGREGATA ROOT; CHINESE CINNAMON; MYRRH; EUCOMMIA ULMOIDES BARK; POLYGALA TENUIFOLIA ROOT; CYPERUS ROTUNDUS ROOT; BOMBYX MORI LARVA; MENTHOL; CLOVE; FRANKINCENSE; PAEONIA VEITCHII ROOT; ANGELICA SINENSIS ROOT; CULLEN CORYLIFOLIUM FRUIT; DOLOMIAEA COSTUS ROOT; ANGELICA DAHURICA ROOT; PRUNUS PERSICA SEED; ASARUM HETEROTROPOIDES VAR. MANDSHURICUM ROOT; BORNEOL; VINCETOXICUM ATRATUM ROOT; LIGUSTICUM SINENSE SUBSP. CHUANXIONG ROOT; TANGERINE PEEL, UNRIPE; CLEMATIS CHINENSIS ROOT; GASTRODIA ELATA TUBER

52784-022

Active ingredient

NOTOGINSENG RADIX RHIZOMA 11%

Purpose

External analgesic

Use

Suitable for sub-healthy people with localized discomfort caused by pain in the neck, shoulder, waist, legs and

joints.[Health effects] It has the health effects of dispersing cold and relieving pain, soothing tendons and

activating blood circulation, removing blood stasis and swelling, and facilitating joints.

Warnings

This product is for external use, prohibit oral use.

Do not use

Skin ulcers, breaks and infections are prohibited.

When using this product

A small number of people have a mild local itching sensation during the use of the product, which does not affect the continued use of the product and can gradually disappear after stopping the use of the product.

Keep out of reach of children.

If swallowed, get medical help or contact a Poison Control Center right away.

Other information

Packed in airtight packaging. Keep in ventilated, dry, protected from light and at room temperature.

Directions

Packed in airtight packaging. Keep in ventilated, dry, protected from light and at room temperature.

Suitable for sub-healthy people with localized discomfort caused by pain in the neck, shoulder, waist, legs and joints.

Inactive ingredients

AUCKLANDIAE RADIX、CARYOPHYLLI FLOS、CINNAMOMI CORTEX、OLIBANUM、MYRRHA、DRACONIS 、SANGUIS、CITRI RETICULATAE PERICARPIUM VIRIDE、PAEONIAE RADIX RUBRA、GASTRODIAE RHIZOMA、GLYCYRRHIZAE RADIX ET , RHIZOMA、LINDERAE RADIX、NOTOPTERYGII RHIZOMA ET RADIX、ACHYRANTHIS BIDENTATAE RADIX、CYNACHI ATRATI RADIX ET RHIZOMA、PERSICAE SEMEN CHUANXIONG RHIZOMA EUCOMMIAE CORTEX、POLYGALAE RADIX CYPERI ,RHIZOMAATRACTYLODIS ,MACROCEPHALAE,RHIZOMA BOMBYX BATRYTICATUS、ANGELICAE SINENSIS RADIX、ASARI RADIX ET RHIZOMA、PSORALEAE FRUCTUS CLEMATIDIS RADIX ET RHIZOMA、TOOSENDAN FRUCTUS、L-MENTHOL、BORNEOLUM SYNTHETICUM,LAUROCAPRAM.